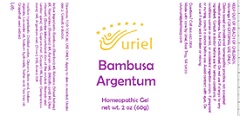 DRUG LABEL: Bambusa Argentum
NDC: 48951-2138 | Form: GEL
Manufacturer: Uriel Pharmacy Inc.
Category: homeopathic | Type: HUMAN OTC DRUG LABEL
Date: 20201222

ACTIVE INGREDIENTS: BAMBUSA VULGARIS WHOLE 8 [hp_X]/1 g; STACHYS OFFICINALIS 8 [hp_X]/1 g; ROSMARINUS OFFICINALIS FLOWERING TOP 8 [hp_X]/1 g; GOLD 9 [hp_X]/1 g; BOS TAURUS INTERVERTEBRAL DISC 10 [hp_X]/1 g; COPPER 11 [hp_X]/1 g; SILICON DIOXIDE 19 [hp_X]/1 g; SILVER 22 [hp_X]/1 g; ARNICA MONTANA 22 [hp_X]/1 g
INACTIVE INGREDIENTS: WATER; SODIUM ALGINATE; LAVENDER OIL; GLYCERIN; SORBIC ACID; CITRUS PARADISI SEED; TEA TREE OIL

Bambusa Argentum

INDICATIONS AND USAGE

Directions: FOR TOPICAL USE ONLY.

DOSAGE AND ADMINISTRATION

Apply to skin as needed. Under age 2: Consult a doctor.

ACTIVE INGREDIENT

Active Ingredients: Bambusa (Bamboo) 8X, Betonica (Wood betony) 8X, Rosmarinus (Rosemary) 8X, Aurum met. (Metallic gold) 9X, Disci intervert. (Bovine intervertebral discs of the cervical, thoracic and lumbar spine) 10X, Cuprum met. (Copper) 11X, Jasper (Semiprecious stone) 19X, Argentum met. (Silver) 22X, Arnica 22X

INACTIVE INGREDIENT

Inactive Ingredients: Distilled water, Glycerin, Boric acid, Sodium alginate, Lavender oil, Sodium hydroxide,
Sorbic acid, Tea tree oil, Grapefruit seed extract

PURPOSE

Use: Temporary relief of headache.

KEEP OUT OF REACH OF CHILDREN.

Warnings: FOR EXTERNAL USE ONLY.
Claims based on traditional homeopathic practice, not accepted medical evidence. Not FDA evaluated.Do not use if allergic to any ingredient. Consult a doctor before use for serious conditions, if conditions worsen or persist, or accidental ingestion occurs. If pregnant or nursing, consult a doctor before use. Avoid contact with eyes. Do not use if safety seal is broken or missing.

Questions? Call 866.642.2858
Made with care by Uriel, East Troy, WI 53120
www.urielpharmacy.com